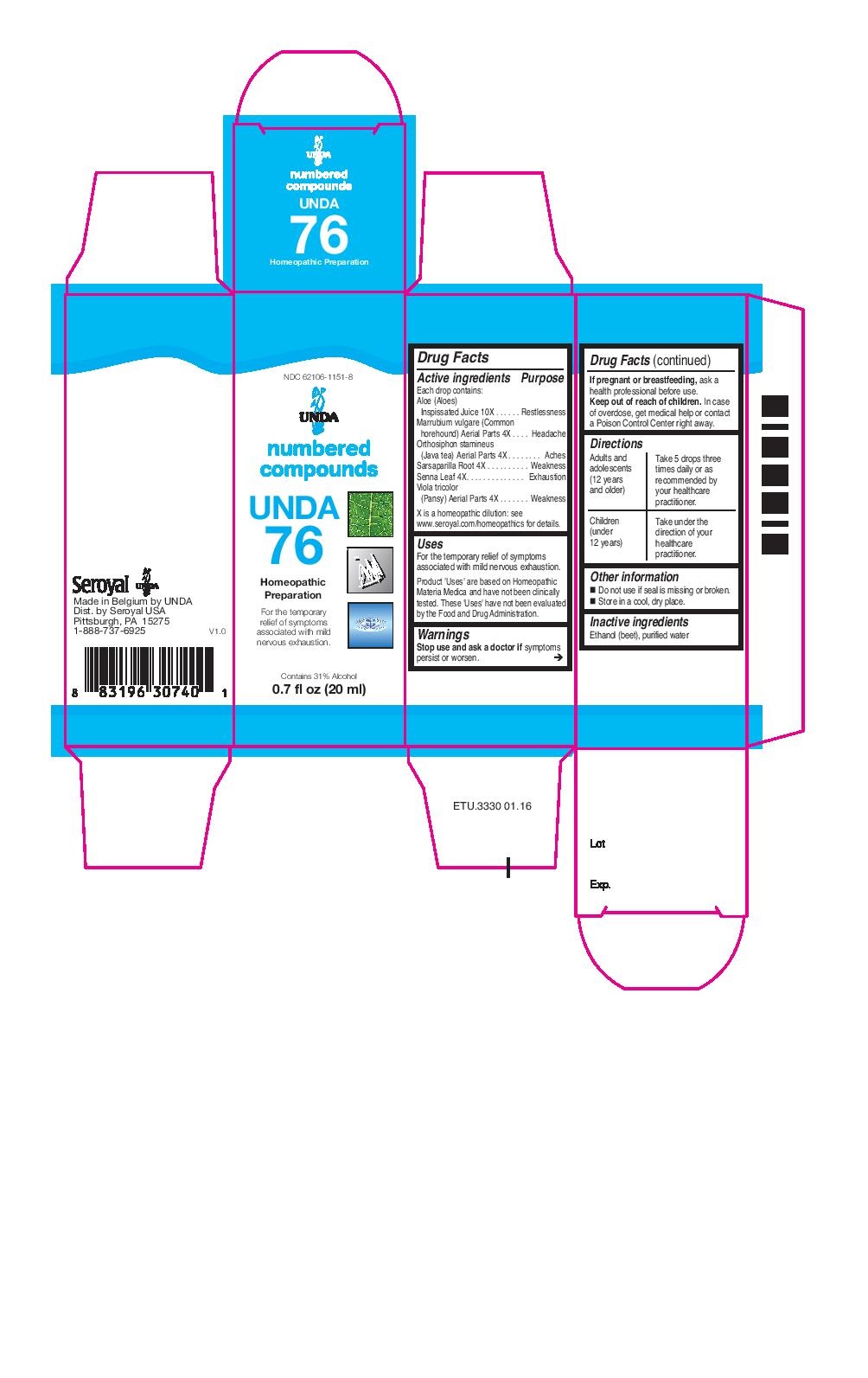 DRUG LABEL: UNDA 76
NDC: 62106-1151 | Form: LIQUID
Manufacturer: Seroyal USA
Category: homeopathic | Type: HUMAN OTC DRUG LABEL
Date: 20221109

ACTIVE INGREDIENTS: MARRUBIUM VULGARE 4 [hp_X]/20 mL; CLERODENDRANTHUS SPICATUS LEAF 4 [hp_X]/20 mL; SARSAPARILLA 4 [hp_X]/20 mL; SENNA LEAF 4 [hp_X]/20 mL; ALOE 10 [hp_X]/20 mL; VIOLA TRICOLOR 4 [hp_X]/20 mL
INACTIVE INGREDIENTS: WATER; ALCOHOL

UNDA 76

Active ingredients
Each drop contains:

Aloe (Aloes) Inspissated Juice 10X
Marrubium vulgare (Common horehound) Aerial Parts 4X
Orthosiphon stamineus (Java tea) Aerial Parts 4X
Sarsaparilla Root 4X
Senna Leaf 4X
Viola tricolor (Pansy) Aerial Parts 4X

Uses
For the temporary relief of symptoms associated with mild nervous exhaustion.

Warnings
Stop use and ask a doctor if symptoms persist or worsen.

If pregnant or breastfeeding, ask a health professional before use.
Keep out of reach of children.

In case of overdose, get medical help or contact a Poison Control Center right away.

PREGNANCY OR BREAST FEEDING

If pregnant or breastfeeding, ask a health professional before use.

Keep out of reach of children.

Other information
Do not use if seal is missing or broken.
Store in a cool, dry place.

Inactive ingredients
Ethanol (beet), purified water

Directions
Adults and adolescents (12 years and older)

Take 5 drops three times daily or as recommended by your healthcare practitioner.

Children (under 12 years)
Take under the direction of your healthcare practitioner.

Uses
For the temporary relief of symptoms associated with mild nervous exhaustion.

Directions
Adults and adolescents (12 years and older)

Take 5 drops three times daily or as recommended by your healthcare practitioner.

Children (under 12 years)
Take under the direction of your healthcare practitioner.

PACKAGE LABEL

NDC 62106-1151-8

UNDA

numbered compounds

UNDA 76

Homeopathic Preparation

For the temporary relief of symptoms associated with mild nervous exhaustion.

Contains 31% Alcohol
0.7 fl oz (20 ml)